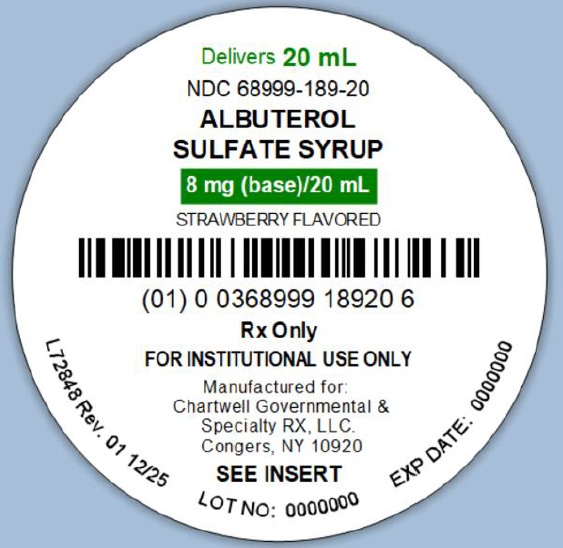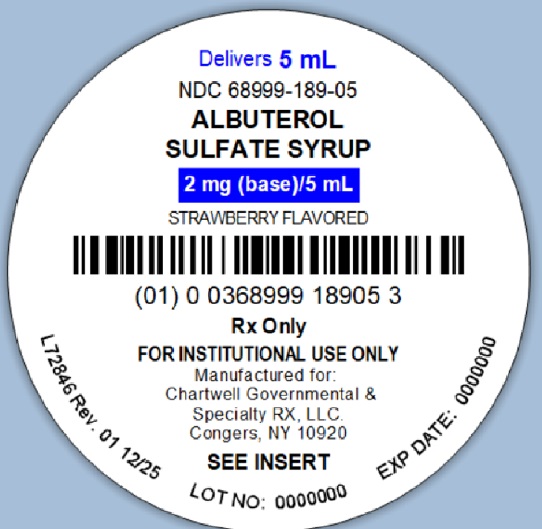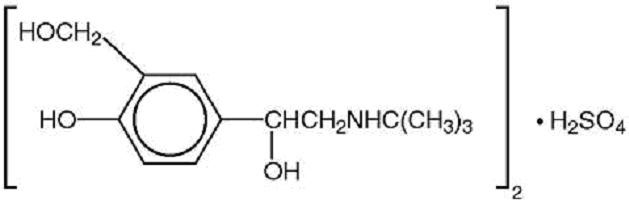 DRUG LABEL: ALBUTEROL SULFATE
NDC: 68999-189 | Form: SYRUP
Manufacturer: Chartwell Governmental & Specialty RX, LLC.
Category: prescription | Type: HUMAN PRESCRIPTION DRUG LABEL
Date: 20251217

ACTIVE INGREDIENTS: ALBUTEROL SULFATE 2 mg/5 mL
INACTIVE INGREDIENTS: HYPROMELLOSE, UNSPECIFIED; ANHYDROUS CITRIC ACID; TRISODIUM CITRATE DIHYDRATE; SODIUM BENZOATE; SORBITOL SOLUTION; FD&C YELLOW NO. 6

ALBUTEROL SULFATE SYRUP
Rx only

DESCRIPTION

Albuterol Sulfate Syrup contains albuterol sulfate, USP, the racemic form of albuterol and a relatively selective beta2-adrenergic bronchodilator. Albuterol sulfate has the chemical name α^1-[(tert-butylamino)methyl]-4-hydroxy- m-xylene-α,α'-diolsulfate (2:1) (salt) and the following chemical structure:

(C13H21NO3)2•H2SO4M.W. 576.7

Albuterol sulfate is a white or practically white powder freely soluble in water and slightly soluble in alcohol, in chloroform, and in ether per USP definition.

The World Health Organization recommended name for albuterol base is salbutamol.

Albuterol Sulfate Syrup for oral administration contains 2 mg of albuterol as 2.4 mg of albuterol sulfate in each teaspoonful (5 mL). Albuterol Sulfate Syrup also contains the inactive ingredients purified water, hypromellose, citric acid anhydrous, sodium citrate dihydrate, sodium benzoate, sorbitol solution, strawberry flavor, and FD&C Yellow # 6. The pH of the syrup is 3.2 to 4.2.

CLINICAL PHARMACOLOGY

In vitrostudies and in vivopharmacologic studies have demonstrated that albuterol has a preferential effect on beta2-adrenergic receptors compared with isoproterenol. While it is recognized that beta2-adrenergic receptors are the predominant receptors in bronchial smooth muscle, data indicate that there is a population of beta2-receptors in the human heart existing in a concentration between 10% and 50%. The precise function of these receptors has not been established (see WARNINGS).

The pharmacologic effects of beta-adrenergic agonist drugs, including albuterol, are at least in part attributable to stimulation through beta-adrenergic receptors of intracellular adenyl cyclase, the enzyme that catalyzes the conversion of adenosine triphosphate (ATP) to cyclic-3', 5'-adenosine monophosphate (cyclic AMP). Increased cyclic AMP levels are associated with relaxation of bronchial smooth muscle and inhibition of release of mediators of immediate hypersensitivity from cells, especially from mast cells.

Albuterol has been shown in most controlled clinical trials to have more effect on the respiratory tract, in the form of bronchial smooth muscle relaxation, than isoproterenol at comparable doses while producing fewer cardiovascular effects.

Albuterol is longer acting than isoproterenol in most patients by any route of administration because it is not a substrate for the cellular uptake processes for catecholamines nor for catechol- O-methyl transferase.

Preclinical

Intravenous studies in rats with albuterol sulfate have demonstrated that albuterol crosses the blood brain barrier and reaches brain concentrations amounting to approximately 5.0% of the plasma concentrations. In structures outside the brain barrier (pineal and pituitary glands), albuterol concentrations were found to be 100 times those in the whole brain.

Studies in laboratory animals (minipigs, rodents, and dogs) have demonstrated the occurrence of cardiac arrhythmias and sudden death (with histologic evidence of myocardial necrosis) when beta-agonists and methylxanthines are administered concurrently. The clinical significance of these findings is unknown.

Pharmacokinetics

Albuterol is rapidly absorbed after oral administration of 10 mL of albuterol sulfate syrup (4 mg of albuterol) in normal volunteers. Maximum plasma concentrations of about 18 ng/mL of albuterol are achieved within 2 hours, and the drug is eliminated with a half-life of about 5 hours.

In other studies, the analysis of urine samples of patients given 8 mg of tritiated albuterol orally showed that 76% of the dose was excreted over three days, with the majority of the dose being excreted within the first 24 hours. Sixty percent of this radioactivity was shown to be the metabolite. Feces collected over this period contained 4% of the administered dose.

Clinical Trials

In controlled clinical trials in patients with asthma, the onset of improvement in pulmonary function, as measured by maximum midexpiratory flow rate (MMEF) and forced expiratory volume in 1 second (FEV1), was within 30 minutes after a dose of albuterol sulfate syrup, with peak improvement occurring between 2 and 3 hours. In a controlled clinical trial involving 55 children, clinically significant improvement (defined as maintaining a 15% or more increase in FEV1and a 20% or more increase in MMEF over baseline values) continued to be recorded up to 6 hours. No decrease in the effectiveness was reported in one uncontrolled study of 32 children who took albuterol sulfate syrup for a 3-month period.

INDICATIONS AND USAGE

Albuterol Sulfate Syrup is indicated for the relief of bronchospasm in adults and children 2 years of age and older with reversible obstructive airway disease.

CONTRAINDICATIONS

Albuterol Sulfate Syrup is contraindicated in patients with a history of hypersensitivity to albuterol or any of its components.

WARNINGS

Cardiovascular Effects

Albuterol Sulfate Syrup, like all other beta-adrenergic agonists, can produce a clinically significant cardiovascular effect in some patients as measured by pulse rate, blood pressure, and/or symptoms. Although such effects are uncommon after administration of albuterol sulfate syrup at recommended doses, if they occur, the drug may need to be discontinued. In addition, beta-agonists have been reported to produce electrocardiogram (ECG) changes, such as flattening of the T wave, prolongation of the QTc interval, and ST segment depression. The clinical significance of these findings is unknown. Therefore, Albuterol Sulfate Syrup, like all sympathomimetic amines, should be used with caution in patients with cardiovascular disorders, especially coronary insufficiency, cardiac arrhythmias, and hypertension.

Deterioration of Asthma

Asthma may deteriorate acutely over a period of hours or chronically over several days or longer. If the patient needs more doses of albuterol sulfate syrup than usual, this may be a marker of destabilization of asthma and requires reevaluation of the patient and treatment regimen, giving special consideration to the possible need for anti-inflammatory treatment, e.g., corticosteroids.

Paradoxical Bronchospasm

Albuterol Sulfate Syrup can produce paradoxical bronchospasm, which may be life threatening. If paradoxical bronchospasm occurs, albuterol sulfate syrup should be discontinued immediately and alternative therapy instituted.

Use of Anti-Inflammatory Agents

The use of beta-adrenergic agonist bronchodilators alone may not be adequate to control asthma in many patients. Early consideration should be given to adding anti-inflammatory agents, e.g., corticosteroids.

Immediate hypersensitivity reactions may occur after administration of albuterol, as demonstrated by rare cases of urticaria, angioedema, rash, bronchospasm, and oropharyngeal edema. Albuterol, like other beta-adrenergic agonists, can produce a significant cardiovascular effect in some patients, as measured by pulse rate, blood pressure, symptoms, and/or electrocardiographic changes.

Rarely, erythema multiforme and Stevens-Johnson syndrome have been associated with the administration of albuterol sulfate in children.

PRECAUTIONS

General

Albuterol, as with all sympathomimetic amines, should be used with caution in patients with cardiovascular disorders, especially coronary insufficiency, cardiac arrhythmias, and hypertension; in patients with convulsive disorders, hyperthyroidism, or diabetes mellitus; and in patients who are unusually responsive to sympathomimetic amines. Clinically significant changes in systolic and diastolic blood pressure have been seen in individual patients and could be expected to occur in some patients after use of any beta-adrenergic bronchodilator.

Large doses of intravenous albuterol have been reported to aggravate preexisting diabetes mellitus and ketoacidosis. As with other beta-agonists, albuterol may produce significant hypokalemia in some patients, possibly through intracellular shunting, which has the potential to produce adverse cardiovascular effects. The decrease is usually transient, not requiring supplementation.

Information for Patients

The action of albuterol sulfate syrup may last up to 6 hours or longer. Albuterol Sulfate Syrup should not be taken more frequently than recommended. Do not increase the dose or frequency of albuterol sulfate syrup without consulting your physician. If you find that treatment with albuterol sulfate syrup becomes less effective for symptomatic relief, your symptoms get worse, and/or you need to take the product more frequently than usual, you should seek medical attention immediately. While you are taking albuterol sulfate syrup, other asthma medications and inhaled drugs should be taken only as directed by your physician. Common adverse effects include palpitations, chest pain, rapid heart rate, and tremor or nervousness. If you are pregnant or nursing, contact your physician about use of albuterol sulfate syrup. Effective and safe use of albuterol sulfate syrup includes an understanding of the way that it should be administered.

Drug Interactions

The concomitant use of albuterol sulfate syrup and other oral sympathomimetic agents is not recommended since such combined use may lead to deleterious cardiovascular effects. This recommendation does not preclude the judicious use of an aerosol bronchodilator of the adrenergic stimulant type in patients receiving albuterol sulfate syrup. Such concomitant use, however, should be individualized and not given on a routine basis. If regular coadministration is required, then alternative therapy should be considered.

Monoamine Oxidase Inhibitors or Tricyclic Antidepressants:Albuterol should be administered with extreme caution to patients being treated with monoamine oxidase inhibitors or tricyclic antidepressants, or within 2 weeks of discontinuation of such agents, because the action of albuterol on the vascular system may be potentiated.

Beta-Blockers:Beta-adrenergic receptor blocking agents not only block the pulmonary effect of beta-agonists, such as albuterol sulfate syrup, but may produce severe bronchospasm in asthmatic patients. Therefore, patients with asthma should not normally be treated with beta-blockers. However, under certain circumstances, e.g., as prophylaxis after myocardial infarction, there may be no acceptable alternatives to the use of beta-adrenergic blocking agents in patients with asthma. In this setting, cardioselective beta-blockers could be considered, although they should be administered with caution.

Diuretics:The ECG changes and/or hypokalemia that may result from the administration of nonpotassium-sparing diuretics (such as loop or thiazide diuretics) can be acutely worsened by beta-agonists, especially when the recommended dose of the beta-agonist is exceeded. Although the clinical significance of these effects is not known, caution is advised in the coadministration of beta-agonists with nonpotassium-sparing diuretics.

Digoxin:Mean decreases of 16% to 22% in serum digoxin levels were demonstrated after single-dose intravenous and oral administration of albuterol, respectively, to normal volunteers who had received digoxin for 10 days. The clinical significance of these findings for patients with obstructive airway disease who are receiving albuterol and digoxin on a chronic basis is unclear. Nevertheless, it would be prudent to carefully evaluate the serum digoxin levels in patients who are currently receiving digoxin and albuterol.

Carcinogenesis, Mutagenesis, Impairment of Fertility

In a 2-year study in Sprague-Dawley rats, albuterol sulfate caused a significant dose-related increase in the incidence of benign leiomyomas of the mesovarium at dietary doses of 2.0, 10, and 50 mg/kg (approximately ½, 2, and 10 times, respectively, the maximum recommended daily oral dose for adults and children, on a mg/m^2basis). In another study this effect was blocked by the coadministration of propranolol, a non-selective beta-adrenergic antagonist. In an 18-month study in CD-1 mice albuterol sulfate showed no evidence of tumorigenicity at dietary doses of up to 500 mg/kg (approximately 60 times the maximum recommended daily oral dose for adults and children on a mg/m^2basis). In a 22-month study in the Golden hamster albuterol sulfate showed no evidence of tumorigenicity at dietary doses of up to 50 mg/kg (approximately 8 times the maximum recommended daily oral dose for adults and children on a mg/m^2basis).

Albuterol sulfate was not mutagenic in the Ames test with or without metabolic activation using tester strains S. typhimuriumTA1537, TA1538, and TA98 or E. coliWP2, WP2uvrA, and WP67. No forward mutation was seen in yeast strain S. cerevisiaeS9 nor any mitotic gene conversion in yeast strain S. cerevisiaeJD1 with or without metabolic activation.

Fluctuation assays in S. typhimuriumTA98 and E. coliWP2, both with metabolic activation, were negative. Albuterol sulfate was not clastogenic in a human peripheral lymphocyte assay or in an AH1 strain mouse micronucleus assay at intraperitoneal doses of up to 200 mg/kg.

Reproduction studies in rats demonstrated no evidence of impaired fertility at oral doses up to 50 mg/kg (approximately 15 times the maximum recommended daily oral dose for adults on a mg/m^2basis).

Pregnancy

Teratogenic Effects

Albuterol has been shown to be teratogenic in mice. A study in CD-1 mice at subcutaneous (sc) doses of 0.025, 0.25, and 2.5 mg/kg (approximately 3/1000, 3/100, and 3/10, respectively, the maximum recommended daily oral dose for adults on a mg/m^2basis), showed cleft palate formation in 5 of 111 (4.5%) fetuses at 0.25 mg/kg and in 10 of 108 (9.3%) fetuses at 2.5 mg/kg. The drug did not induce cleft palate formation at the lowest dose, 0.025 mg/kg. Cleft palate also occurred in 22 of 72 (30.5%) fetuses from females treated with 2.5 mg/kg of isoproterenol (positive control) subcutaneously (approximately 3/10 times the maximum recommended daily oral dose for adults on a mg/m^2basis).

A reproduction study in Stride Dutch rabbits revealed cranioschisis in 7 of 19 (37%) fetuses when albuterol was administered orally at a 50 mg/kg dose (approximately 25 times the maximum recommended daily oral dose for adults on a mg/m^2basis).

There are no adequate and well-controlled studies in pregnant women. Albuterol should be used during pregnancy only if the potential benefit justifies the potential risk to the fetus.

During worldwide marketing experience, various congenital anomalies, including cleft palate and limb defects, have been rarely reported in the offspring of patients being treated with albuterol. Some of the mothers were taking multiple medications during their pregnancies. No consistent pattern of defects can be discerned, and a relationship between albuterol use and congenital anomalies has not been established.

Use in Labor and Delivery

Because of the potential for beta-agonist interference with uterine contractility, use of albuterol sulfate syrup for relief of bronchospasm during labor should be restricted to those patients in whom the benefits clearly outweigh the risk.

Tocolysis:Albuterol has not been approved for the management of preterm labor. The benefit : risk ratio when albuterol is administered for tocolysis has not been established. Serious adverse reactions, including maternal pulmonary edema, have been reported during or following treatment of premature labor with beta2-agonists, including albuterol.

Nursing Mothers

It is not known whether this drug is excreted in human milk. Because of the potential for tumorigenicity shown for albuterol in some animal studies, a decision should be made whether to discontinue nursing or to discontinue the drug, taking into account the importance of the drug to the mother.

Pediatric Use

Safety and effectiveness in children below 2 years of age have not been established.

ADVERSE REACTIONS

In clinical trials, the most frequent adverse reactions to albuterol sulfate syrup in adults and older children were:

Percent Incidence of Adverse Reactions in Adults and Children (6-14 Years of Age)
Reaction | Percent Incidence
Central nervous system
Tremor | 10%
Nervousness | 9%
Shakiness | 9%
Headache | 4%
Dizziness | 3%
Hyperactivity | 2%
Excitement | 2%
Sleeplessness | 1%
Disturbed sleep | <1%
Irritable behavior | <1%
Dilated pupils | <1%
Weakness | <1%
Cardiovascular
Tachycardia | 1%
Palpitations | <1%
Sweating | <1%
Chest pain | <1%
Ear, nose, and throat
Epistaxis | 1%
Gastrointestinal
Increased appetite | 3%
Epigastric pain | <1%
Stomachache | <1%
Musculoskeletal
Muscle spasm | <1%
Respiratory
Cough | <1%

In clinical trials, the following adverse reactions to albuterol sulfate syrup were noted more frequently in young children 2 to 6 years of age than in older children and adults:

Percent Incidence of Adverse Reactions Noted More Frequently in Children 2 to 6 Years of Age Than in Older Children and Adults
Reaction | Percent Incidence
Central nervous system
Excitement | 20%
Nervousness | 15%
Hyperkinesia | 4%
Sleeplessness | 2%
Emotional lability | 1%
Fatigue | 1%
Cardiovascular
Tachycardia | 2%
Pallor | 1%
Gastrointestinal
Gastrointestinal symptoms | 2%
Loss of Appetite | 1%
Ophthalmologic
Conjunctivitis | 1%

Cases of urticaria, angioedema, rash, bronchospasm, hoarseness, oropharyngeal edema, and arrhythmias (including atrial fibrillation, supraventricular tachycardia, extrasystoles) have been reported after the use of albuterol sulfate syrup.

In addition, albuterol, like other sympathomimetic agents, can cause adverse reactions such as hypertension, angina, vomiting, vertigo, central nervous system stimulation, unusual taste, and drying or irritation of the oropharynx.

The reactions are generally transient in nature, and it is usually not necessary to discontinue treatment with albuterol sulfate syrup. In selected cases, however, dosage may be reduced temporarily; after the reaction has subsided, dosage should be increased in small increments to the optimal dosage.

OVERDOSAGE

The expected symptoms with overdosage are those of excessive beta-adrenergic stimulation and/or occurrence or exaggeration of any of the symptoms listed under ADVERSE REACTIONS,e.g., seizures, angina, hypertension or hypotension, tachycardia with rates up to 200 beats per minute, arrhythmias, nervousness, headache, tremor, dry mouth, palpitation, nausea, dizziness, fatigue, malaise, and sleeplessness. Hypokalemia may also occur. As with all sympathomimetic medications, cardiac arrest and even death may be associated with abuse of albuterol sulfate syrup. Treatment consists of discontinuation of albuterol sulfate syrup together with appropriate symptomatic therapy. The judicious use of a cardioselective beta-receptor blocker may be considered, bearing in mind that such medication can produce bronchospasm. There is insufficient evidence to determine if dialysis is beneficial for overdosage of albuterol sulfate syrup.

The oral median lethal dose of albuterol sulfate in mice is greater than 2000 mg/kg (approximately 240 times the maximum recommended daily oral dose for adults and children on a mg/m^2basis). In mature rats the subcutaneous (sc) median lethal dose of albuterol sulfate is approximately 450 mg/kg (approximately 110 times the maximum recommended daily oral dose for adults and children on a mg/m^2basis). In small young rats the oral median lethal dose is approximately 2000 mg/kg (approximately 480 times the maximum recommended daily oral dose for adults and children on a mg/m^2basis).

DOSAGE AND ADMINISTRATION

The following dosages of albuterol sulfate syrup are expressed in terms of albuterol base.

Usual Dosage

Adults and Children Over 14 Years of Age:

The usual starting dosage for adults and children over 14 years of age is 2 mg (1 teaspoonful) or 4 mg (2 teaspoonfuls) three or four times a day.

Children Over 6 Years to 14 Years of Age:

The usual starting dosage for children over 6 years to 14 years of age is 2 mg (1 teaspoonful) three or four times a day.

Children 2 to 5 Years of Age:

Dosing in children 2 to 5 years of age should be initiated at 0.1 mg/kg of body weight three times a day. This starting dosage should not exceed 2 mg (1 teaspoonful) three times a day.

Dosage Adjustment

Adults and Children Over 14 Years of Age:

For adults and children over 14 years of age, a dosage above 4 mg four times a day should be used only when the patient fails to respond. If a favorable response does not occur with the 4-mg initial dosage, it should be cautiously increased stepwise up to a maximum of 8 mg four times a day as tolerated.

Children Over 6 Years to 14 Years of Age Who Fail to Respond to the Initial Starting Dosage of 2 mg Four Times a Day:

For children over 6 years to 14 years of age who fail to respond to the initial starting dosage of 2 mg four times a day, the dosage may be cautiously increased stepwise, but not to exceed 24 mg/day (given in divided doses).

Children 2 to 5 Years of Age Who Do Not Respond Satisfactorily to the Initial Dosage:

For children from 2 to 5 years of age who do not respond satisfactorily to the initial starting dosage, the dosage may be increased stepwise to 0.2 mg/kg of body weight three times a day, but not to exceed a maximum of 4 mg (2 teaspoonfuls) given three times a day.

Elderly Patients and Those Sensitive to Beta-adrenergic Stimulators:

The initial dosage should be restricted to 2 mg three or four times a day and individually adjusted thereafter.

HOW SUPPLIED

Albuterol Sulfate Syrup, a clear, orange-yellow liquid with a strawberry flavor, contains 2 mg of albuterol (present as the sulfate) per 5 mL and is supplied in the following containers:
5 mL Unit-Dose Cup NDC 68999-189-05
20 Unit-Dose Cups of 5 mL each NDC 68999-189-24
20 mL Unit-Dose Cup NDC 68999-189-20
20 Unit-Dose Cups of 20 mL each NDC 68999-189-23
Store at 20° to 25°C (68° to 77°F) [See USP Controlled Room Temperature].

Manufactured for:
Chartwell Governmental & Specialty RX, LLC.
Congers, NY 10920

Rev 12/2025

L72850

PACKAGE LABEL.PRINCIPAL DISPLAY PANEL

ALBUTEROL SULFATE SYRUP - NDC 68999-189-05 - 5 mL Unit-Dose Cup Label

ALBUTEROL SULFATE SYRUP - NDC 68999-189-20 - 20 mL Unit-Dose Cup Label